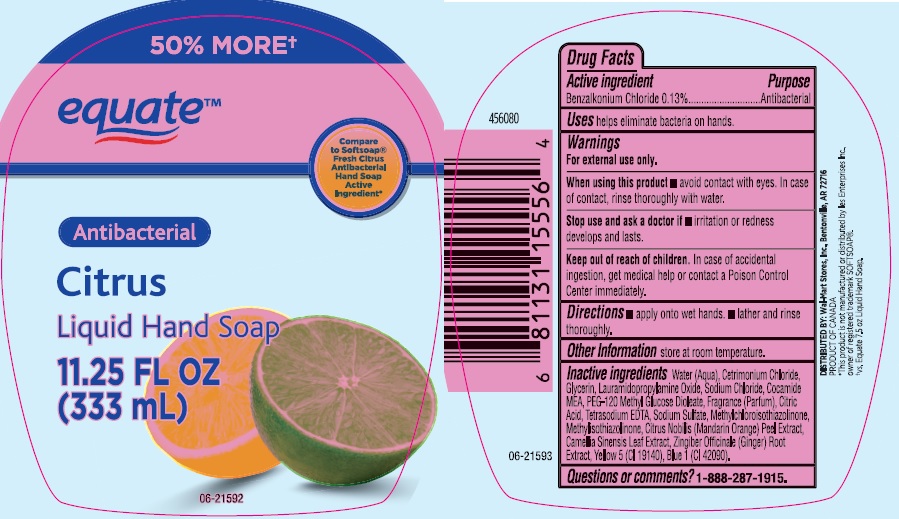 DRUG LABEL: Equate Antibacterial Citrus Hand
NDC: 49035-701 | Form: LIQUID
Manufacturer: Wal-Mart Store Inc
Category: otc | Type: HUMAN OTC DRUG LABEL
Date: 20170106

ACTIVE INGREDIENTS: BENZALKONIUM CHLORIDE 1.3 mg/1 mL
INACTIVE INGREDIENTS: WATER; CETRIMONIUM CHLORIDE; GLYCERIN; LAURAMIDOPROPYLAMINE OXIDE; SODIUM CHLORIDE; COCO MONOETHANOLAMIDE; PEG-120 METHYL GLUCOSE DIOLEATE; CITRIC ACID ACETATE; EDETATE SODIUM; SODIUM SULFATE; METHYLCHLOROISOTHIAZOLINONE; METHYLISOTHIAZOLINONE; TANGERINE PEEL; GREEN TEA LEAF; GINGER; FD&C YELLOW NO. 5; FD&C BLUE NO. 1

Drug Facts

Active ingredient

Benzalkonium Chloride 0.13%

Purpose

Antibacterial

Uses

helps eliminate bacteria on hands.

Warnings

For external use only.

When using this product

- avoid contact with eyes. In case of contact, rinse thoroughly with water.

Stop use and ask a doctor if

- irritation or redness develops and lasts.

Keep out of reach of children.

In case of accidental ingestion, get medical help or contact a Poison Control Center immediately.

Directions

- apply onto wet hands.
- lather and rinse thoroughly.

Other information

store at room temperature.

Inactive ingredients

Water (Aqua), Cetrimonium Chloride, Glycerin, Lauramidopropylamine Oxide, Sodium Chloride, Cocamide MEA, PEG-120 Methyl Glucose Dioleate, Fragrance (Parfum), Citric Acid, Tetrasodium EDTA, Sodium Sulfate, Methylchloroisothiazolinone, Methylisothiazolinone, Citrus Nobilis (Mandarin Orange) Peel Extract, Camellia Sinensis Leaf Extract, Zingiber Officinale (Ginger) Root Extract, Yellow 5 (CI 19140), Blue 1 (CI 42090).

Questions or comments?

1-888-287-1915